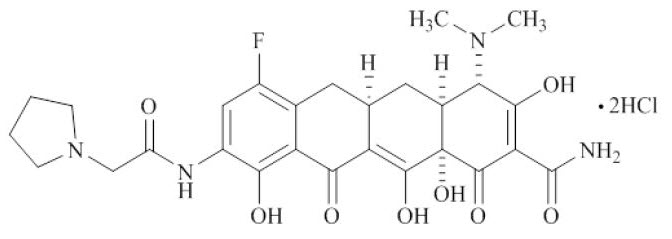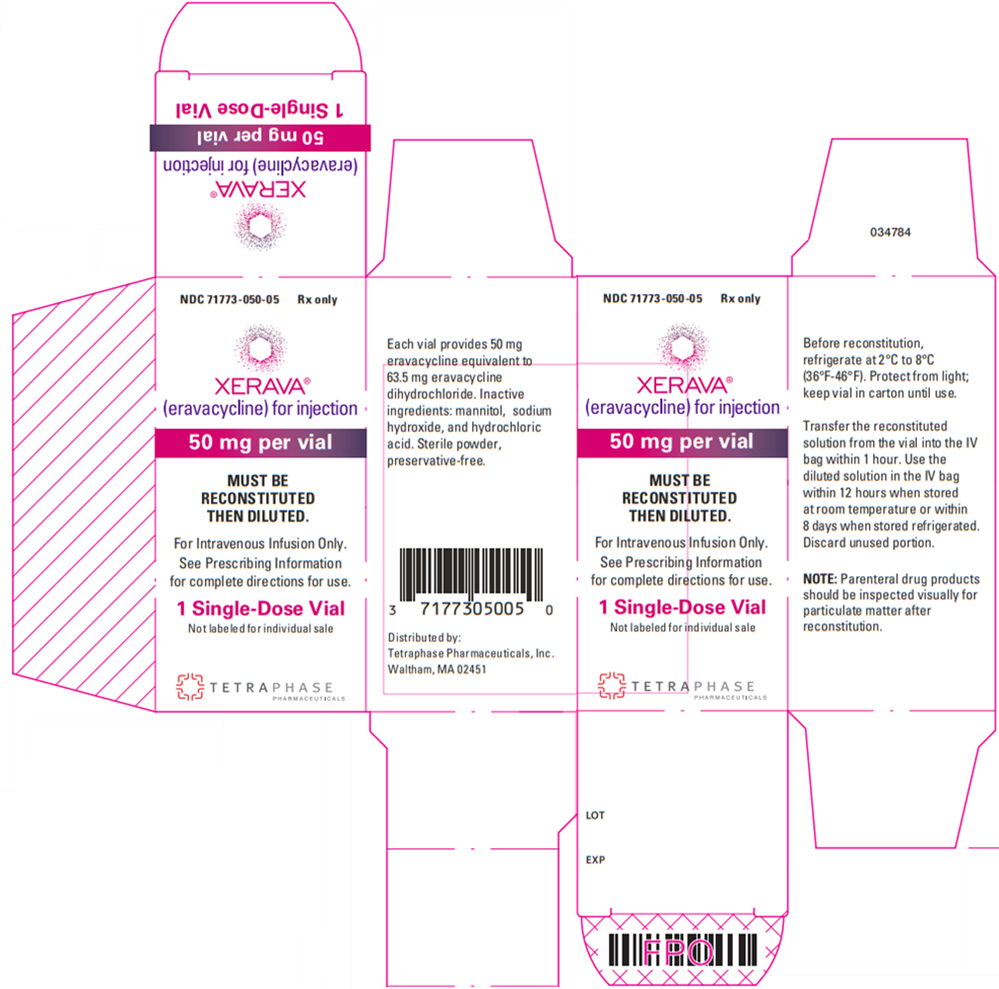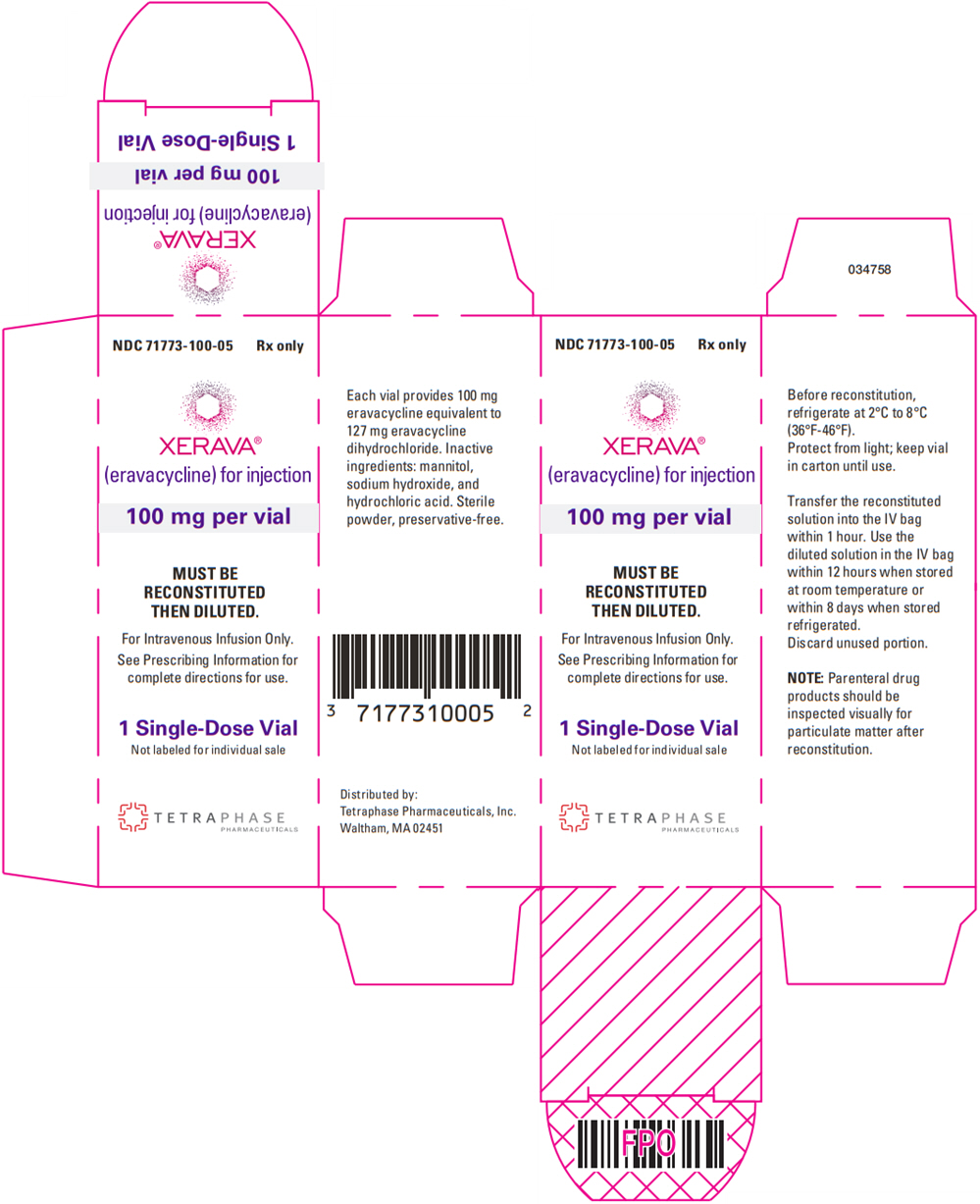 DRUG LABEL: Xerava
NDC: 71773-050 | Form: INJECTION, POWDER, LYOPHILIZED, FOR SOLUTION
Manufacturer: Tetraphase Pharmaceuticals, Inc.
Category: prescription | Type: HUMAN PRESCRIPTION DRUG LABEL
Date: 20250922

ACTIVE INGREDIENTS: ERAVACYCLINE DIHYDROCHLORIDE 50 mg/1 1
INACTIVE INGREDIENTS: MANNITOL; SODIUM HYDROXIDE; HYDROCHLORIC ACID

HIGHLIGHTS OF PRESCRIBING INFORMATION

These highlights do not include all the information needed to use XERAVA safely and effectively. See full prescribing information for XERAVA.
XERAVA® (eravacycline) for injection, for intravenous use
Initial U.S. Approval: 2018

RECENT MAJOR CHANGES

Dosage and Administration (2.4) | 12/2024
Warnings and Precautions, Tetracycline Class Adverse Reactions (5.5) | 3/2025

1 INDICATIONS AND USAGE

XERAVA is a tetracycline class antibacterial indicated for the treatment of complicated intra‑abdominal infections in patients 18 years of age and older. (1.1)

Limitations of Use
XERAVA is not indicated for the treatment of complicated urinary tract infections (cUTI). (1.1)

To reduce the development of drug-resistant bacteria and maintain the effectiveness of XERAVA and other antibacterial drugs, XERAVA should be used only to treat or prevent infections that are proven or strongly suspected to be caused by susceptible bacteria. (1.2)

2 DOSAGE AND ADMINISTRATION

- Administer XERAVA for injection 1 mg/kg by intravenous infusion over approximately 60 minutes every 12 hours for a total duration of 4 to 14 days. (2.1)
- Severe Hepatic Impairment (Child Pugh C): 1 mg/kg XERAVA every 12 hours on Day 1, then 1 mg/kg every 24 hours starting on Day 2 for a total duration of 4 to 14 days. (2.2)
- Concomitant Use of a Strong Cytochrome P450 (CYP) Isoenzyme 3A Inducer: 1.5 mg/kg XERAVA every 12 hours for a total duration of 4 to 14 days. (2.3)
- See full prescribing information for the preparation of XERAVA. (2.4)

3 DOSAGE FORMS AND STRENGTHS

- For injection: 50 mg and 100 mg of eravacycline (equivalent to 63.5 mg and 127 mg eravacycline dihydrochloride, respectively) as a lyophilized powder in a single-dose vial for reconstitution and further dilution. (3)

4 CONTRAINDICATIONS

Known hypersensitivity to eravacycline, tetracycline-class antibacterial drugs, or any of the excipients in XERAVA. (4, 5, 6)

5 WARNINGS AND PRECAUTIONS

- Hypersensitivity Reactions: Life-threatening hypersensitivity (anaphylactic) reactions have been reported with tetracycline antibacterial drugs, including XERAVA. Avoid use in patients with known hypersensitivity to tetracyclines. (5.1)
- Tooth Discoloration and Enamel Hypoplasia: The use of XERAVA during tooth development (last half of pregnancy, infancy and childhood to the age of 8 years) may cause permanent discoloration of the teeth (yellow-gray-brown) and enamel hypoplasia. (5.2, 8.1, 8.4)
- Inhibition of Bone Growth: The use of XERAVA during the second and third trimester of pregnancy, infancy and childhood up to the age of 8 years may cause reversible inhibition of bone growth. (5.3, 8.1, 8.4)
- Clostridioides difficile-Associated Diarrhea: Evaluate if diarrhea occurs. (5.4)

6 ADVERSE REACTIONS

Most common adverse reactions (incidence ≥ 3%) are infusion site reactions, nausea, and vomiting. (6.1)

To report SUSPECTED ADVERSE REACTIONS, contact Tetraphase Pharmaceuticals, Inc., at 1-800-651-3861 or FDA at 1-800-FDA-1088 or www.fda.gov/medwatch.

7 DRUG INTERACTIONS

- Strong CYP 3A Inducers: Co-administration decreases the exposure of eravacycline; increase XERAVA dose with concomitant use. (2.3, 7.1, 12.3)
- Anticoagulant Drugs: Downward adjustment of anticoagulant dosage may be required. (7.2)

8 USE IN SPECIFIC POPULATIONS

Lactation: Breastfeeding is not recommended during treatment with XERAVA. (8.2)

FULL PRESCRIBING INFORMATION

1 INDICATIONS AND USAGE

1.1 Complicated Intra-abdominal Infections

XERAVA is indicated for the treatment of complicated intra‑abdominal infections (cIAI) caused by susceptible microorganisms: Escherichia coli, Klebsiella pneumoniae, Citrobacter freundii, Enterobacter cloacae, Klebsiella oxytoca, Enterococcus faecalis, Enterococcus faecium, Staphylococcus aureus, Streptococcus anginosus group, Clostridium perfringens, Bacteroides species, and Parabacteroides distasonis in patients 18 years or older [see Microbiology (12.4) and Clinical Studies (14.1)].

Limitations of Use

XERAVA is not indicated for the treatment of complicated urinary tract infections (cUTI) [see Clinical Studies (14.2)].

1.2 Usage

To reduce the development of drug-resistant bacteria and maintain the effectiveness of XERAVA and other antibacterial drugs, XERAVA should be used only to treat or prevent infections that are proven or strongly suspected to be caused by susceptible bacteria. When culture and susceptibility information are available, they should be considered in selecting or modifying antibacterial therapy. In the absence of such data, local epidemiology and susceptibility patterns may contribute to the empiric selection of therapy.

2 DOSAGE AND ADMINISTRATION

2.1 Recommended Adult Dosage

The recommended dose regimen of XERAVA is 1 mg/kg every 12 hours. Administer intravenous infusions of XERAVA over approximately 60 minutes every 12 hours.

The recommended duration of treatment with XERAVA for cIAI is 4 to 14 days. The duration of therapy should be guided by the severity and location of infection and the patient's clinical response.

2.2 Dosage Modifications in Patients with Hepatic Impairment

In patients with severe hepatic impairment (Child Pugh C), administer XERAVA 1 mg/kg every 12 hours on Day 1 followed by XERAVA 1 mg/kg every 24 hours starting on Day 2 for a total duration of 4 to 14 days. No dosage adjustment is warranted in patients with mild to moderate hepatic impairment (Child Pugh A and Child Pugh B) [see Use in Specific Populations (8.6) and Clinical Pharmacology (12.3)].

2.3 Dosage Modifications in Patients with Concomitant Use of a Strong Cytochrome P450 (CYP) Isoenzyme 3A Inducer

With concomitant use of a strong CYP3A inducer, administer XERAVA 1.5 mg/kg every 12 hours for a total duration of 4 to 14 days. No dosage adjustment is warranted in patients with concomitant use of a weak or moderate CYP3A inducer [see Drug Interactions (7.1) and Clinical Pharmacology (12.3)].

2.4 Preparation and Administration

XERAVA is for intravenous infusion only. Each vial is for a single dose only.

Preparation

XERAVA is supplied as a sterile yellow to orange dry powder in a single-dose vial that must be reconstituted and further diluted prior to intravenous infusion as outlined below. XERAVA does not contain preservatives. Aseptic technique must be used for reconstitution and dilution as follows:

1. Calculate the dose of XERAVA based on the patient weight (1 mg/kg actual body weight). Prepare the required dose for intravenous infusion by reconstituting the appropriate number of vials needed. Reconstitute each vial of XERAVA with 5 mL of Sterile Water for Injection, USP or with 5 mL of 0.9% Sodium Chloride Injection, USP, which will deliver the following:
  - XERAVA 50 mg vial will deliver 50 mg (10 mg/mL) of eravacycline (free base equivalents).
  - XERAVA 100 mg vial will deliver 100 mg (20 mg/mL) of eravacycline (free base equivalents).
2. Swirl the vial gently until the powder has dissolved entirely. Avoid shaking or rapid movement as it may cause foaming. The reconstituted XERAVA solution should be a clear, pale yellow to orange solution. Do not use the solution if you notice any particles or the solution is cloudy. Reconstituted solution is not for direct injection. The stability of the solution after reconstitution in the vial has been demonstrated for 1 hour at room temperature (not to exceed 25°C/77°F). If the reconstituted solution in the vial is not diluted in the infusion bag within 1 hour, the reconstituted vial content must be discarded.
3. The reconstituted XERAVA solution is further diluted for intravenous infusion to a target concentration of 0.3 mg/mL, in a 0.9% Sodium Chloride Injection, USP infusion bag before intravenous infusion. To dilute the reconstituted solution, withdraw the full or partial reconstituted vial content from each vial and add it into the infusion bag to generate an infusion solution with a target concentration of 0.3 mg/mL (within a range of 0.2 to 0.6 mg/mL). Do not shake the bag.
4. The diluted solutions must be infused within 12 hours if stored at room temperature (not to exceed 25°C/77°F) or within 8 days if stored refrigerated at 2°C to 8°C (36°F to 46°F). Reconstituted XERAVA solutions and diluted XERAVA infusion solutions should not be frozen.
5. Visually inspect the diluted XERAVA solution for particulate matter and discoloration prior to administration (the XERAVA infusion solution for administration is clear and ranges from light yellow to orange). Discard unused portions of the reconstituted and diluted solution.

Administration of the Intravenous Infusion

The diluted XERAVA solution is administered as an intravenous infusion over approximately 60 minutes.

XERAVA may be administered intravenously through a dedicated line or through a Y-site. If the same intravenous line is used for sequential infusion of several drugs, the line should be flushed before and after infusion of XERAVA with 0.9% Sodium Chloride Injection, USP.

2.5 Drug Compatibilities

XERAVA is compatible with 0.9% Sodium Chloride Injection, USP. The compatibility of XERAVA with other drugs and infusion solutions has not been established. XERAVA should not be mixed with other drugs or added to solutions containing other drugs.

3 DOSAGE FORMS AND STRENGTHS

XERAVA for injection is a yellow to orange, sterile, preservative-free, lyophilized powder in single-dose vials for reconstitution and further dilution. XERAVA is available in two strengths:

- 50 mg of eravacycline (equivalent to 63.5 mg eravacycline dihydrochloride)
- 100 mg of eravacycline (equivalent to 127 mg eravacycline dihydrochloride)

4 CONTRAINDICATIONS

XERAVA is contraindicated for use in patients with known hypersensitivity to eravacycline, tetracycline-class antibacterial drugs, or to any of the excipients [see Warnings and Precautions (5.1) and Adverse Reactions (6.1)].

5 WARNINGS AND PRECAUTIONS

5.1 Hypersensitivity Reactions

Life-threatening hypersensitivity (anaphylactic) reactions have been reported with XERAVA [see Adverse Reactions (6.1)]. XERAVA is structurally similar to other tetracycline-class antibacterial drugs and should be avoided in patients with known hypersensitivity to tetracycline- class antibacterial drugs. Discontinue XERAVA if an allergic reaction occurs.

5.2 Tooth Discoloration and Enamel Hypoplasia

The use of XERAVA during tooth development (last half of pregnancy, infancy and childhood to the age of 8 years) may cause permanent discoloration of the teeth (yellow-grey-brown). This adverse reaction is more common during long-term use of the tetracycline class drugs, but it has been observed following repeated short-term courses. Enamel hypoplasia has also been reported with tetracycline class drugs. Advise the patient of the potential risk to the fetus if XERAVA is used during the second or third trimester of pregnancy [see Use in Specific Populations (8.1, 8.4)].

5.3 Inhibition of Bone Growth

The use of XERAVA during the second and third trimester of pregnancy, infancy and childhood up to the age of 8 years may cause reversible inhibition of bone growth. All tetracyclines form a stable calcium complex in any bone-forming tissue. A decrease in fibula growth rate has been observed in premature infants given oral tetracycline in doses of 25 mg/kg every 6 hours. This reaction was shown to be reversible when the drug was discontinued. Advise the patient of the potential risk to the fetus if XERAVA is used during the second or third trimester of pregnancy [see Use in Specific Populations (8.1, 8.4)].

5.4 Clostridioides difficile-Associated Diarrhea

Clostridioides difficile associated diarrhea (CDAD) has been reported with use of nearly all antibacterial agents and may range in severity from mild diarrhea to fatal colitis. Treatment with antibacterial agents alters the normal flora of the colon leading to overgrowth of C. difficile.

C. difficile produces toxins A and B which contribute to the development of CDAD. Hypertoxin producing strains of C. difficile cause increased morbidity and mortality, as these infections can be refractory to antimicrobial therapy and may require colectomy. CDAD must be considered in all patients who present with diarrhea following antibacterial drug use. Careful medical history is necessary since CDAD has been reported to occur over two months after the administration of antibacterial agents.

If CDAD is suspected or confirmed, ongoing antibacterial drug use not directed against C. difficile may need to be discontinued. Appropriate fluid and electrolyte management, protein supplementation, antibacterial drug treatment of C. difficile, and surgical evaluation should be instituted as clinically indicated.

5.5 Tetracycline Class Adverse Reactions

XERAVA is structurally similar to tetracycline-class antibacterial drugs and may have similar adverse reactions. Adverse reactions including photosensitivity, fixed drug eruption, pseudotumor cerebri, and anti‑ anabolic action which has led to increased BUN, azotemia, acidosis, hyperphosphatemia, pancreatitis, and abnormal liver function tests, have been reported for other tetracycline-class antibacterial drugs, and may occur with XERAVA. Discontinue XERAVA if any of these adverse reactions is suspected.

5.6 Potential for Microbial Overgrowth

XERAVA use may result in overgrowth of non-susceptible organisms, including fungi. If such infections occur, discontinue XERAVA and institute appropriate therapy.

5.7 Development of Drug-Resistant Bacteria

Prescribing XERAVA in the absence of a proven or strongly suspected bacterial infection is unlikely to provide benefit to the patient and increases the risk of the development of drug-resistant bacteria [see Indications and Usage (1.2)].

6 ADVERSE REACTIONS

The following clinically significant adverse reactions are described in greater detail in the Warnings and Precautions section:

- Hypersensitivity Reactions [Warning and Precautions (5.1)]
- Tooth Discoloration [Warning and Precautions (5.2)]
- Inhibition of Bone Growth [Warning and Precautions (5.3)]
- Clostridioides difficile-Associated Diarrhea [Warning and Precautions (5.4)]
- Tetracycline Class Adverse Reactions [Warning and Precautions (5.5)]

6.1 Clinical Trials Experience

Because clinical trials are conducted under widely varying conditions, adverse reaction rates observed in the clinical trials of a drug cannot be directly compared to rates in the clinical trials of another drug and may not reflect the rates observed in practice.

XERAVA was evaluated in 3 active-controlled clinical trials (Trial 1, Trial 2, and Trial 3) in adults with cIAI. These trials included two Phase 3 trials (Trial 1 and Trial 2) and one Phase 2 trial (Trial 3, NCT01265784). The Phase 3 trials included 520 patients treated with XERAVA and 517 patients treated with comparator antibacterial drugs (ertapenem or meropenem). The median age of patients treated with XERAVA was 56 years, ranging between 18 and 93 years old; 30% were age 65 years and older. Patients treated with XERAVA were predominantly male (57%) and Caucasian (98%). The XERAVA-treated population included 31% obese patients (BMI ≥ 30 kg/m2) and 8% with baseline moderate to severe renal impairment (calculated creatinine clearance 15 to less than 60 mL/min). Among the trials, 66 (13%) of patients had baseline moderate hepatic impairment (Child Pugh B); patients with severe hepatic impairment (Child Pugh C) were excluded from the trials.

Adverse Reactions Leading to Discontinuation

Treatment discontinuation due to an adverse reaction occurred in 2% (11/520) of patients receiving XERAVA and 2% (11/517) of patients receiving the comparator. The most commonly reported adverse reactions leading to discontinuation of XERAVA were related to gastrointestinal disorders.

Most Common Adverse Reactions

Adverse reactions occurring at 3% or greater in patients receiving XERAVA were infusion site reactions, nausea, and vomiting.

Table 1 lists adverse reactions occurring in ≥ 1% of patients receiving XERAVA and with incidences greater than the comparator in the Phase 3 cIAI clinical trials. A similar adverse reaction profile was observed in the Phase 2 cIAI clinical trial (Trial 3).

Table 1: Selected Adverse Reactions Reported in ≥ 1% of Patients Receiving XERAVA in the Phase 3 cIAI Trials (Trial 1 and Trial 2)
Adverse Reactions | XERAVA [XERAVA dose equals 1 mg/kg every 12 hours IV.] N=520 n (%) | Comparators [Comparators include ertapenem 1 g every 24 hours IV and meropenem 1 g every 8 hours IV.] N=517 n (%)
Infusion site reactions [Infusion site reactions include: catheter/vessel puncture site pain, infusion site extravasation, infusion site hypoaesthesia, infusion/injection site phlebitis, infusion site thrombosis, injection site/vessel puncture site erythema, phlebitis, phlebitis superficial, thrombophlebitis, and vessel puncture site swelling.] | 40 (7.7) | 10 (1.9)
Nausea | 34 (6.5) | 3 (0.6)
Vomiting | 19 (3.7) | 13 (2.5)
Diarrhea | 12 (2.3) | 8 (1.5)
Hypotension | 7 (1.3) | 2 (0.4)
Wound dehiscence | 7 (1.3) | 1 (0.2)
Abbreviations: IV=intravenous

Other Adverse Reactions of XERAVA

The following selected adverse reactions were reported in XERAVA-treated patients at a rate of less than 1% in the Phase 3 trials:

Cardiac disorders: palpitations

Gastrointestinal System: acute pancreatitis, pancreatic necrosis

General Disorders and Administrative Site Conditions: chest pain

Immune system disorders: hypersensitivity

Laboratory Investigations: increased amylase, increased lipase, increased alanine aminotransferase, prolonged activated partial thromboplastin time, decreased renal clearance of creatinine, increased gamma-glutamyltransferase, decreased white blood cell count, neutropenia

Metabolism and nutrition disorders: hypocalcemia

Nervous System: dizziness, dysgeusia

Psychiatric disorders: anxiety, insomnia, depression

Respiratory, Thoracic, and Mediastinal System: pleural effusion, dyspnea

Skin and subcutaneous tissue disorders: rash, hyperhidrosis

7 DRUG INTERACTIONS

7.1 Effect of Other Drugs on XERAVA

Strong CYP3A Inducers

Concomitant use of strong CYP3A inducers decreases the exposure of eravacycline, which may reduce the efficacy of XERAVA [see Clinical Pharmacology (12.3)]. Increase XERAVA dose in patients with concomitant use of a strong CYP3A inducer [see Dosage and Administration (2.3)].

7.2 Effect of XERAVA on other Drugs

Anticoagulant Drugs

Because tetracyclines have been shown to depress plasma prothrombin activity, patients who are on anticoagulant therapy may require downward adjustment of their anticoagulant dosage.

8 USE IN SPECIFIC POPULATIONS

8.1 Pregnancy

Risk Summary

XERAVA, like other tetracycline-class antibacterial drugs, may cause discoloration of deciduous teeth and reversible inhibition of bone growth when administered during the second and third trimester of pregnancy [see Warnings and Precautions (5.1, 5.2), Use in Specific Populations (8.4)]. The limited available data with XERAVA use in pregnant women are insufficient to inform drug‑associated risk of major birth defects and miscarriages. Animal studies indicate that eravacycline crosses the placenta and is found in fetal plasma; doses greater than approximately 3- and 2.8- times the clinical exposure, based on AUC in rats and rabbits, respectively, administered during the period of organogenesis, were associated with decreased ossification, decreased fetal body weight, and/or increased post-implantation loss (see Data).

The estimated background risk of major birth defects and miscarriage for the indicated population is unknown. All pregnancies have a background risk of birth defect, loss, or other adverse outcomes. In the U.S. general population, the estimated background risk of major birth defects and miscarriage in clinically recognized pregnancies is 2 to 4% and 15 to 20%, respectively.

Data

Animal Data

Embryo-fetal development studies in rats and rabbits reported no treatment-related effects at approximately 3 and 2.8 times the clinical exposure (based on AUC). Dosing was during the period of organogenesis, i.e., gestation days 7-17 in rats and gestation days 7-19 in rabbits. Higher doses, approximately 8.6 and 6.3 times the clinical exposure (based on AUC) in rats and rabbits, respectively, were associated with fetal effects including increased post-implantation loss, reduced fetal body weights, and delays in skeletal ossification in both species, and abortion in the rabbit.

A peri-natal and post-natal rat toxicity study demonstrated that eravacycline crosses the placenta and is found in fetal plasma following intravenous administration to the dams. This study did not demonstrate anatomical malformations, but there were early decreases in pup weight that were later comparable to controls and a non-significant trend toward increased stillbirths or dead pups during lactation. F1 males from dams treated with 10 mg/kg/day eravacycline that continued to fertility testing had decreased testis and epididymis weights at approximately post-natal day 111 that may have been at least partially related to lower body weights in this group.

Tetracyclines cross the placenta, are found in fetal tissues, and can have toxic effects on the developing fetus (often related to retardation of skeletal development). Evidence of embryotoxicity also has been noted in animals treated early in pregnancy.

8.2 Lactation

Risk Summary

It is not known whether XERAVA is excreted in human breast milk. Eravacycline (and its metabolites) is excreted in the milk of lactating rats (see Data). Tetracyclines are excreted in human milk; however, the extent of absorption of tetracyclines, including eravacycline, by the breastfed infant is not known. There are no data on the effects of XERAVA on the breastfed infant, or the effects on milk production. Because there are other antibacterial drug options available to treat cIAI in lactating women and because of the potential for serious adverse reactions, including tooth discoloration and inhibition of bone growth, advise patients that breastfeeding is not recommended during treatment with XERAVA and for 4 days (based on half-life) after the last dose.

Data

Animal Data

Eravacycline (and its metabolites) was excreted in the milk of lactating rats on post-natal day 15 following intravenous administration of 3, 5, and 10 mg/kg/day eravacycline.

8.3 Females and Males of Reproductive Potential

Infertility

Based on animal studies, XERAVA can lead to impaired spermiation and sperm maturation, resulting in abnormal sperm morphology and poor motility. The effect is reversible in rats. The long-term effects of XERAVA on male fertility have not been studied [see Nonclinical Toxicology (13.1)].

8.4 Pediatric Use

The safety and effectiveness of XERAVA in pediatric patients have not been established.

Due to the adverse effects of the tetracycline-class of drugs, including XERAVA on tooth development and bone growth, use of XERAVA in pediatric patients less than 8 years of age is not recommended [see Warnings and Precautions (5.1, 5.2)].

8.5 Geriatric Use

Of the total number of patients with cIAI who received XERAVA in Phase 3 clinical trials (n = 520), 158 subjects were ≥ 65 years of age, while 59 subjects were ≥ 75 years of age. No overall differences in safety or efficacy were observed between these subjects and younger subjects.

No clinically relevant differences in the pharmacokinetics of eravacycline were observed with respect to age in a population pharmacokinetic analysis of eravacycline [see Clinical Pharmacology (12.3)].

8.6 Hepatic Impairment

No dosage adjustment is warranted for XERAVA in patients with mild to moderate hepatic impairment (Child Pugh A and Child Pugh B). Adjust XERAVA dosage in patients with severe hepatic impairment (Child Pugh C) [see Dosage and Administration (2.2) and Clinical Pharmacology (12.3)].

8.7 Renal Impairment

No dosage adjustment is necessary for XERAVA in patients with renal impairment [see Clinical Pharmacology (12.3)].

10 OVERDOSAGE

No reports of overdose were reported in clinical trials. In the case of suspected overdose, XERAVA should be discontinued and the patient monitored for adverse reactions. Hemodialysis is not expected to remove significant quantities of XERAVA [see Clinical Pharmacology (12.3)].

11 DESCRIPTION

XERAVA contains eravacycline, a synthetic tetracycline-class antibacterial agent for intravenous administration. Chemically, eravacycline is a C7-, C9-substituted sancycline derivative. The chemical name of eravacycline dihydrochloride is [(4S,4aS,5aR,12aS)-4-(dimethylamino)-7-fluoro-3,10,12,12a-tetrahydroxy-1,11-dioxo-9-[2‑(pyrrolidin-1-yl) acetamido]-1,4,4a,5,5a,6,11,12a-octahydrotetracene-2-carboxamide] dihydrochloride. The molecular formula for eravacycline dihydrochloride is C27H31FN4O8•2HCl, and its molecular weight is 631.5.

The following represents the chemical structure of eravacycline dihydrochloride:

XERAVA is a sterile, preservative-free, yellow to orange, lyophilized powder in a glass single-dose vial for intravenous infusion after reconstitution and dilution. XERAVA is supplied in two (2) strengths as follows:

- Each 50 mg single-dose vial contains 50 mg of eravacycline (equivalent to 63.5 mg of eravacycline dihydrochloride) and the excipient, mannitol (150 mg). Sodium hydroxide and hydrochloric acid are used as needed for pH adjustment to 5.5 to 7.0.
- Each 100 mg single-dose vial contains 100 mg of eravacycline (equivalent to 127 mg of eravacycline dihydrochloride) and the excipient, mannitol (150 mg). Sodium hydroxide and hydrochloric acid are used as needed for pH adjustment to 5.5 to 7.0.

The amount of sodium in XERAVA lyophilized powder is negligible. Following reconstitution and dilution to a target concentration of 0.3 mg/mL in 0.9% Sodium Chloride Injection, USP, each XERAVA dose would contain 3.54 mg/mL of sodium [see Dosage and Administration (2.4)].

12 CLINICAL PHARMACOLOGY

12.1 Mechanism of Action

Eravacycline is an antibacterial drug [see Microbiology (12.4)].

12.2 Pharmacodynamics

The AUC divided by the MIC of eravacycline has been shown to be the best predictor of activity. Based on the flat exposure-response relationship observed in clinical studies, eravacycline exposure achieved with the recommended dosage regimen appears to be on the plateau of the exposure-response curve.

Cardiac Electrophysiology

The effect of XERAVA on the QTc interval was evaluated in a Phase 1 randomized, placebo and positive controlled, double-blind, single-dose, crossover thorough QTc study in 60 healthy adult subjects. At the 1.5 mg/kg single dose (1.5 times the maximum approved recommended dose), XERAVA did not prolong the QTc interval to any clinically relevant extent.

12.3 Pharmacokinetics

Following single-dose intravenous administration, eravacycline AUC and Cmax increase approximately dose-proportionally over doses from 1 mg/kg to 3 mg/kg (3 times the approved dose).

The mean exposure of eravacycline after single and multiple intravenous infusions (approximately 60 minutes) of 1 mg/kg administered to healthy adults every 12 hours is presented in Table 2.

There is approximately 45% accumulation following intravenous dosing of 1 mg/kg every 12 hours.

Table 2: Mean (%CV) Plasma Exposure of Eravacycline After Single and Multiple Intravenous Dose in Healthy Adults
 | Exposure [Arithmetic Mean (%CV)]
 | Cmax (ng/mL) | AUC0-12 (ng∙h/mL)
Day 1 | 2125 (15) | 4305 (14) [AUC of day 1 equals AUC0-12 after the first dose of eravacycline.]
Day 10 | 1825 (16) | 6309 (15) [AUC of day 10 equals steady state AUC0-12.]
Abbreviations: Cmax = maximum observed plasma concentration, CV = coefficient of variation; AUC0-12 = area under the plasma concentration-time curve from time 0 to 12 hours.

Distribution

Protein binding of eravacycline to human plasma proteins increases with increasing plasma concentrations, with 79% to 90% (bound) at plasma concentrations ranging from 100 to 10,000 ng/mL. The volume of distribution at steady-state is approximately 321 L.

Elimination

The mean elimination half-life is 20 hours.

Metabolism

Eravacycline is metabolized primarily by CYP3A4- and FMO-mediated oxidation.

Excretion

Following a single intravenous dose of radiolabeled eravacycline 60 mg, approximately 34% of the dose is excreted in urine and 47% in feces as unchanged eravacycline (20% in urine and 17% in feces) and metabolites.

Specific Populations

No clinically significant differences in the pharmacokinetics of eravacycline were observed based on age (18-86 years), sex, and race.

Patients with Renal Impairment

The geometric least square mean Cmax for eravacycline was increased by 8.8% for subjects with end stage renal disease (ESRD) versus healthy subjects with 90% CI -19.4, 45.2. The geometric least square mean AUC0-inf for eravacycline was decreased by 4.0% for subjects with ESRD versus healthy subjects with 90% CI -14.0, 12.3 [see Use in Specific Populations (8.7)].

Patients with Hepatic Impairment

Eravacycline Cmax was 13.9%, 16.3%, and 19.7% higher in subjects with mild (Child-Pugh Class A), moderate (Child-Pugh Class B), and severe (Child‑Pugh Class C) hepatic impairment versus healthy subjects, respectively. Eravacycline AUC0-inf was 22.9%, 37.9%, and 110.3% higher in subjects with mild, moderate, and severe hepatic impairment versus healthy subjects, respectively [see Dosage and Administration (2.2) and Use in Specific Populations (8.6)].

Drug Interaction Studies

Clinical Studies

Concomitant use of rifampin (strong CYP3A4/3A5 inducer) decreased eravacycline AUC by 35% and increased eravacycline clearance by 54% [see Dosage and Administration (2.3) and Drug Interactions (7.1)].

Concomitant use of itraconazole (strong CYP3A inhibitor) increased eravacycline Cmax by 5% and AUC0-t by 32%, and decreased eravacycline clearance by 32%.

In Vitro Studies

Eravacycline is a substrate for the transporters P-gp, organic anion transporter peptide OATP1B1 and OATP1B3

Eravacycline is not a substrate for breast cancer resistance protein (BCRP), bile salt export pump (BSEP), organic ion transporter (OAT)1, OAT3, OCT1, OCT2, multidrug and toxin extrusion (protein) (MATE)1, or MATE2-K transporters.

Eravacycline is not an inhibitor of BCRP, BSEP, OATP1B1, OATP1B3, OAT1, OAT3, OCT1, OCT2, MATE1, or MATE2-K transporters.

Eravacycline is not an inhibitor of CYP1A2, 2B6, 2C8, 2C9, 2C19, 2D6, or 3A4/5. Eravacycline is not an inducer of CYP1A2, 2B6, or 3A4.

12.4 Microbiology

Mechanism of Action

Eravacycline is a fluorocycline antibacterial within the tetracycline class of antibacterial drugs. Eravacycline disrupts bacterial protein synthesis by binding to the 30S ribosomal subunit thus preventing the incorporation of amino acid residues into elongating peptide chains.

In general, eravacycline is bacteriostatic against gram-positive bacteria (e.g., Staphylococcus aureus and Enterococcus faecalis); however, in vitro bactericidal activity has been demonstrated against certain strains of Escherichia coli and Klebsiella pneumoniae.

Resistance

Eravacycline resistance in some bacteria is associated with upregulated, non-specific intrinsic multidrug-resistant (MDR) efflux, and target-site modifications such as to the 16s rRNA or certain 30S ribosomal proteins (e.g., S10).

The C7 and C9 substitutions in eravacycline are not present in any naturally occurring or semisynthetic tetracyclines and the substitution pattern imparts microbiological activities including in vitro activity against gram-positive and gram-negative strains expressing certain tetracycline-specific resistance mechanism(s) [i.e., efflux mediated by tet(A), tet(B), and tet(K); ribosomal protection as encoded by tet(M) and tet(Q)].

Activity of eravacycline was demonstrated in vitro against Enterobacteriaceae in the presence of certain beta-lactamases, including extended spectrum β-lactamases, and AmpC. However, some beta-lactamase-producing isolates may confer resistance to eravacycline via other resistance mechanisms.

The overall frequency of spontaneous mutants in the gram-positive organisms tested was in the range of 10^-9 to 10^-10 at 4 times the eravacycline Minimum Inhibitory Concentration (MIC). Multistep selection of gram-negative strains resulted in a 16- to 32-times increase in eravacycline MIC for one isolate of Escherichia coli and Klebsiella pneumoniae, respectively. The frequency of spontaneous mutations in K. pneumoniae was 10^-7 to 10^‑8 at 4 times the eravacycline MIC.

Interaction with Other Antimicrobials

In vitro studies have not demonstrated antagonism between XERAVA and other commonly used antibacterial drugs for the indicated pathogens.

Antimicrobial Activity

XERAVA has been shown to be active against most isolates of the following microorganisms, both in vitro and in clinical infections [see Indications and Usage (1)]:

Aerobic bacteria

Gram-positive bacteria

Enterococcus faecalis
Enterococcus faecium
Staphylococcus aureus
Streptococcus anginosus group

Gram-negative bacteria
Citrobacter freundii
Enterobacter cloacae
Escherichia coli
Klebsiella oxytoca
Klebsiella pneumoniae

Anaerobic bacteria
Gram-positive bacteria
Clostridium perfringens

Gram-negative bacteria
Bacteroides caccae
Bacteroides fragilis
Bacteroides ovatus
Bacteroides thetaiotaomicron
Bacteroides uniformis
Bacteroides vulgatus
Parabacteroides distasonis

The following in vitro data are available, but their clinical significance is unknown. At least 90 percent of the following bacteria exhibit an in vitro minimum inhibitory concentration (MIC) less than or equal to the susceptible breakpoint for eravacycline against isolates of similar genus or organism group. However, the efficacy of eravacycline in treating clinical infections caused by these bacteria has not been established in adequate and well-controlled clinical trials.

Aerobic bacteria

Gram-positive bacteria
Streptococcus salivarius group

Gram-negative bacteria
Citrobacter koseri
Enterobacter aerogenes

Susceptibility Test Methods

For specific information regarding susceptibility test interpretive criteria, and associated test methods and quality control standards recognized by FDA for this drug, please see https://www.fda.gov/STIC.

13 NONCLINICAL TOXICOLOGY

13.1 Carcinogenesis, Mutagenesis, Impairment of Fertility

Carcinogenicity studies with eravacycline have not been conducted. However, there has been evidence of oncogenic activity in rats in studies with the related antibacterial drugs, oxytetracycline (adrenal and pituitary tumors) and minocycline (thyroid tumors).

Eravacycline was not genotoxic in a standard battery of assays, including an in vitro mammalian cell mutation assay, an in vitro clastogenicity assay, and an in vivo rat bone marrow micronucleus assay.

There are no human data on the effect of eravacycline on fertility. Eravacycline did not affect mating or fertility in male rats following intravenous administration at a dose approximating a clinical dose of 0.65 mg/kg/day (approximately 1.5 times the clinical exposure, based on AUC determined in a separate study), however, eravacycline administration at higher doses was associated with adverse reactions on male fertility and spermatogenesis that were at least partially reversible after a 70-day recovery period (1 spermatogenic cycle). Decreased sperm counts, abnormal sperm morphology, and reduced sperm motility were observed with testicular effects (impaired spermiation and sperm maturation). There were no adverse reactions on mating or fertility in female rats administered intravenous eravacycline at a dose approximating a clinical dose of 3.2 mg/kg/day (approximately 18 times the clinical exposure based on AUC determined in a separate study in unmated females).

Decreased sperm counts and eravacycline‑related lesions noted in the testes and epididymides were seen in general toxicology studies in rats and were reversible. These findings were anticipated effects for a tetracycline-class compound.

13.2 Animal Toxicology and/or Pharmacology

In repeated dose toxicity studies in rats, dogs and monkeys, lymphoid depletion/atrophy of lymph nodes, spleen and thymus, decreased erythrocytes, reticulocytes, leukocytes, and platelets (dog and monkey), in association with bone marrow hypocellularity, and adverse gastrointestinal effects (dog and monkey) were observed with eravacycline. These findings were reversible or partially reversible during recovery periods of 3 to 7 weeks.

Bone discoloration, which was not fully reversible over recovery periods of up to 7 weeks, was observed in rats and monkeys after 13 weeks of dosing and in the juvenile rat study after dosing over post-natal days 21-70.

Intravenous administration of eravacycline has been associated with a histamine response in rat and dog studies.

14 CLINICAL STUDIES

14.1 Complicated Intra-abdominal Infections in Adults

A total of 1,041 adults hospitalized with cIAI were enrolled in two Phase 3, randomized, double-blind, active-controlled, multinational, multicenter trials (Trial 1, NCT01844856, and Trial 2, NCT02784704). These studies compared XERAVA (1 mg/kg intravenous every 12 hours) with either ertapenem (1 g every 24 hours) or meropenem (1 g every 8 hours) as the active comparator for 4 to 14 days of therapy. Complicated intra-abdominal infections included appendicitis, cholecystitis, diverticulitis, gastric/duodenal perforation, intra-abdominal abscess, perforation of intestine, and peritonitis.

The microbiologic intent-to-treat (micro-ITT) population, which included all patients who had at least one baseline intra-abdominal pathogen, consisted of 846 patients in the two trials. Populations in Trial 1 and Trial 2 were similar. The median age was 56 years and 56% were male. The majority of patients (95%) were from Europe; 5% were from the United States. The most common primary cIAI diagnosis was intra-abdominal abscess(es), occurring in 60% of patients. Bacteremia at baseline was present in 8% of patients.

Clinical cure was defined as complete resolution or significant improvement of signs or symptoms of the index infection at the Test of Cure (TOC) visit which occurred 25 to 31 days after randomization. Selected clinical responses were reviewed by a Surgical Adjudication Committee. Table 3 presents the clinical cure rates in the micro-ITT population. Clinical cure rates at the TOC visit for selected pathogens are presented in Table 4.

Table 3: Clinical Cure Rates at TOC in the Phase 3 cIAI Trials, Micro-ITT Population
 | Trial 1 |  | Trial 2
 | XERAVA [XERAVA dose equals 1 mg/kg every 12 hours IV.] N=220 n (%) | Ertapenem [Ertapenem dose equals1 g every 24 hours IV.] N=226 n (%) | XERAVA N=195 n (%) | Meropenem [Meropenem dose equals 1 g every 8 hours IV.] N=205 n (%)
Clinical cure | 191 (86.8) | 198 (87.6) | 177 (90.8) | 187 (91.2)
Difference (95% CI) [Treatment Difference = Difference in clinical cure rates (eravacycline minus ertapenem or meropenem). Confidence intervals are calculated using the unadjusted Miettinen-Nurminen method.] | -0.80 (-7.1, 5.5) |  | -0.5 (-6.3, 5.3)
Abbreviations: CI = confidence interval; IV = intravenous; micro-ITT = all randomized subjects who had baseline bacterial pathogens that caused cIAI and against at least one of which the investigational drug has in vitro antibacterial activity; N = number of subjects in the micro-ITT population; n = number within a specific category with a clinical cure based on the Surgical Adjudication Committee assessment (if available); TOC = Test of Cure.

Table 4: Clinical Cure Rates at TOC by Selected Baseline Pathogens in Pooled Phase 3 cIAI Trials, Micro-ITT Population
Pathogen | XERAVA [XERAVA dose equals 1 mg/kg every 12 hours IV.] N=415 n/N1 (%) | Comparators [Comparators include Ertapenem 1 g every 24 hours IV and Meropenem 1 g every 8 hours IV.] N=431 n/N1 (%)
Enterobacteriaceae | 271/314 (86.3) | 289/325 (88.9)
Citrobacter freundii | 19/22 (86.4) | 8/10 (80.0)
Enterobacter cloacae complex | 17/21 (81.0) | 23/24 (95.8)
Escherichia coli | 220/253 (87.0) | 237/266 (89.1)
Klebsiella oxytoca | 14/15 (93.3) | 16/19 (84.2)
Klebsiella pneumoniae | 37/39 (94.9) | 42/50 (84.0)
Enterococcus faecalis | 45/54 (83.3) | 47/54 (87.0)
Enterococcus faecium | 38/45 (84.4) | 48/53 (90.6)
Staphylococcus aureus | 24/24 (100.0) | 12/14 (85.7)
Streptococcus anginosus group [Includes Streptococcus anginosus, Streptococcus constellatus, and Streptococcus intermedius] | 79/92 (85.9) | 50/59 (84.7)
Anaerobes [Includes Bacteroides caccae, Bacteroides fragilis, Bacteroides ovatus, Bacteroides thetaiotaomicron, Bacteroides uniformis, Bacteroides vulgatus, Clostridium perfringens, and Parabacteroides distasonis.] | 186/215 (86.5) | 194/214 (90.7)
Abbreviations: IV = intravenous; N = Number of subjects in the micro-ITT Population; N1 = Number of subjects with a specific pathogen; n = Number of subjects with a clinical cure at the TOC visit. Percentages are calculated as 100 × (n/N1); TOC = Test of Cure

14.2 Complicated Urinary Tract Infections (cUTI) in Adults

Two randomized, double-blind, active-controlled, clinical trials (Trial 4, NCT01978938, and Trial 5, NCT03032510) evaluated the efficacy and safety of once-daily intravenous eravacycline for the treatment of patients with complicated urinary tract infections (cUTI). Trial 4 included an optional switch from IV to oral therapy with eravacycline. The trials did not demonstrate the efficacy of XERAVA for the combined endpoints of clinical cure and microbiological success in the microbiological intent-to-treat (micro-ITT) population at the test-of-cure visit [see Indications and Usage (1)].

16 HOW SUPPLIED/STORAGE AND HANDLING

16.1 How Supplied

XERAVA (eravacycline) for injection is a yellow to orange, sterile, preservative-free powder for reconstitution in single-dose 10-mL clear glass vials with a rubber stopper and an aluminum overseal. XERAVA is supplied in the following configurations:

- XERAVA 50 mg vial contains 50 mg of eravacycline (equivalent to 63.5 mg of eravacycline dihydrochloride). Each vial is packaged in a single-dose vial carton (NDC 71773-050-05) and supplied in a 12-vial carton containing 12 single-dose vial cartons— NDC 71773-050-12.
- XERAVA 100 mg vial contains 100 mg of eravacycline (equivalent to 127 mg of eravacycline dihydrochloride). Each vial is packaged in a single-dose vial carton (NDC 71773-100-05) and supplied in shrink wrap packaging, containing 12 single-dose vial cartons— NDC 71773-100-12.

16.2 Storage and Handling

Prior to reconstitution, XERAVA should be stored at 2°C to 8°C (36°F to 46°F) [see Dosage and Administration (2.4)]. Keep vial in carton until use.

17 PATIENT COUNSELING INFORMATION

Serious Allergic Reactions

Advise patients that allergic reactions, including serious allergic reactions, could occur and that serious reactions require immediate treatment. Ask patient about any previous hypersensitivity reactions to antibacterial drugs including tetracycline or other allergens [see Warnings and Precautions (5.1)].

Tooth Discoloration and Inhibition of Bone Growth

Advise patients that XERAVA, like other tetracycline-class drugs, may cause permanent tooth discoloration of deciduous teeth and reversible inhibition of bone growth when administered during the second and third trimesters of pregnancy. Advise patients that they should tell their healthcare provider right away if they become pregnant [see Warnings and Precautions (5.2, 5.3) and Use in Specific Populations (8.1, 8.4)].

Lactation

Advise women not to breastfeed during treatment with XERAVA and for 4 days after the last dose [see Use in Specific Populations (8.2)].

Diarrhea

Diarrhea is a common problem caused by antibacterial drugs, including XERAVA, which usually ends when the antibacterial drug is discontinued. Sometimes after starting treatment with antibacterial drug, patients can develop watery and bloody stools (with or without stomach cramps and fever) which may be a sign of a more serious intestinal infection, even as late as 2 or more months after having taken the last dose of the antibacterial drug. If this occurs, instruct patients to contact their healthcare provider as soon as possible [see Warnings and Precautions (5.4)].

Tetracycline Class Adverse Reactions

Inform patients that XERAVA is similar to tetracycline-class antibacterial drugs and may have similar adverse reactions [see Warnings and Precautions (5.5)].

Overgrowth of Non-susceptible Microorganisms

Inform patients that antibacterial drugs including XERAVA may promote the overgrowth of non-susceptible microorganisms, including fungi [see Warnings and Precautions (5.6)].

Antibacterial Resistance

Patients should be counseled that antibacterial drugs including XERAVA should only be used to treat bacterial infections. They do not treat viral infections (for example, the common cold). When XERAVA is prescribed to treat a bacterial infection, patients should be told that although it is common to feel better early in the course of therapy, the medication should be taken exactly as directed. Skipping doses or not completing the full course of therapy may (1) decrease the effectiveness of the immediate treatment and (2) increase the likelihood that bacteria will develop resistance and will not be treatable by XERAVA or other antibacterial drugs in the future.

Distributed by:
Tetraphase Pharmaceuticals, Inc.
Waltham, MA 02451

XERAVA is a registered trademark of Tetraphase Pharmaceuticals, Inc.
©2025 Tetraphase Pharmaceuticals, Inc. All rights reserved.

PRINCIPAL DISPLAY PANEL - 50 mg Vial Carton

NDC 71773-050-05
Rx only

XERAVA®
(eravacycline) for injection

50 mg per vial

MUST BE
RECONSTITUTED
THEN DILUTED.

For Intravenous Infusion Only.
See Prescribing Information
for complete directions for use.

1 Single-Dose Vial
Not labeled for individual sale

TETRAPHASE
PHARMACEUTICALS

PRINCIPAL DISPLAY PANEL - 100 mg Vial Carton

NDC 71773-100-05
Rx only

XERAVA®
(eravacycline) for injection

100 mg per vial

MUST BE
RECONSTITUTED
THEN DILUTED.

For Intravenous Infusion Only.
See Prescribing Information for
complete directions for use.

1 Single-Dose Vial
Not labeled for Individual sale

TETRAPHASE
PHARMACEUTICALS